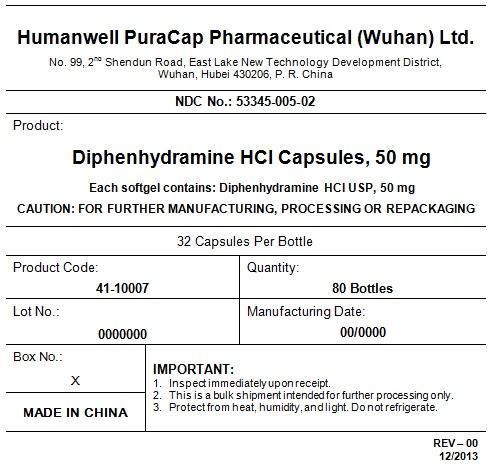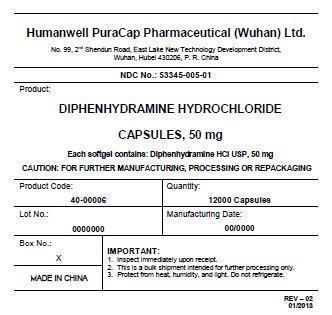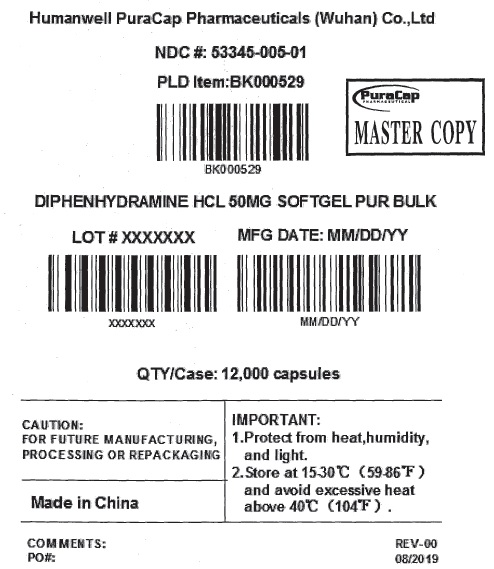 DRUG LABEL: DIPHENHYDRAMINE HYDROCHLORIDE
NDC: 53345-005 | Form: CAPSULE, LIQUID FILLED
Manufacturer: Humanwell PuraCap Pharmaceutical (Wuhan), Ltd.
Category: otc | Type: HUMAN OTC DRUG LABEL
Date: 20241120

ACTIVE INGREDIENTS: DIPHENHYDRAMINE HYDROCHLORIDE 50 mg/1 1
INACTIVE INGREDIENTS: FD&C BLUE NO. 1; GELATIN; GLYCERIN; POLYETHYLENE GLYCOL, UNSPECIFIED; WATER; SORBITOL

DIPHENHYDRAMINE HYDROCHLORIDE 50 mg capsule, liquid filled

Drug Facts

Active ingredient (in each capsule)

Diphenhydramine HCl 50 mg

Purpose

Nighttime sleep-aid

Uses

- for the relief of occasional sleeplessness

Warnings

DO NOT USE

- do not give to children under 12 years of age
- do not usewith any other product containing diphenhydramine, even one used on skin

Ask a doctor before use if you have

- a breathing problem such as emphysema or chronic bronchitis
- glaucoma
- trouble urinating due to an enlarged prostate gland

Ask a doctor or pharmacist before use if you aretaking sedatives or tranquilizers.

When using this productavoid alcoholic drinks.

Stop use and ask a doctor if

- sleeplessness persist continuously for more than 2 weeks. Insomnia may be a symptom of serious underlying medical illness.

PREGNANCY OR BREAST FEEDING

If pregnant or breast-feeding,ask a health professional before use.

Keep out of reach of children.In case of overdose, get medical help or contact a Poison Control Center right away.

Directions

- adults and children 12 years of age and over:1 softgel (50 mg) at bedtime if needed, or as directed by a doctor.

Other information

- store at room temperature 15°-30°C (59°-86°F) and avoid excessive heat
- do not use if imprinted safety seal under cap is broken or missing

Inactive ingredients

FD&C blue #1, gelatin, glycerin, polyethylene glycol, purified water, sorbitol special and white edible ink.

Manufactured by:
Humanwell PuraCap Pharmaceutical (Wuhan) Ltd.
Wuhan, Hubei
430206, China

PRINCIPAL DISPLAY PANEL - Shipping Label

DIPHENHYDRAMINE HYDROCHLORIDE CAPSULES, 50 mg

Quantity : 12000 Capsules
NDC. No : 53345-005-01

IMPORTANT:

Inspect immediate upon receipt.
This is a bulk shipment intended for further processing only.
Protect from heat, humidity, and light. Do not refrigerate.

CAUTION : "FOR FURTHER MANUFACTURING, PROCESSING OR REPACKING"

PRINCIPAL DISPLAY PANEL - Shipping Label

DIPHENHYDRAMINE HYDROCHLORIDE CAPSULES, 50 mg

Quantity : 80 Bottles
NDC. No : 53345-005-02

IMPORTANT:

Inspect immediate upon receipt.
This is a bulk shipment intended for further processing only.
Protect from heat, humidity, and light. Do not refrigerate.

CAUTION : "FOR FURTHER MANUFACTURING, PROCESSING OR REPACKING"